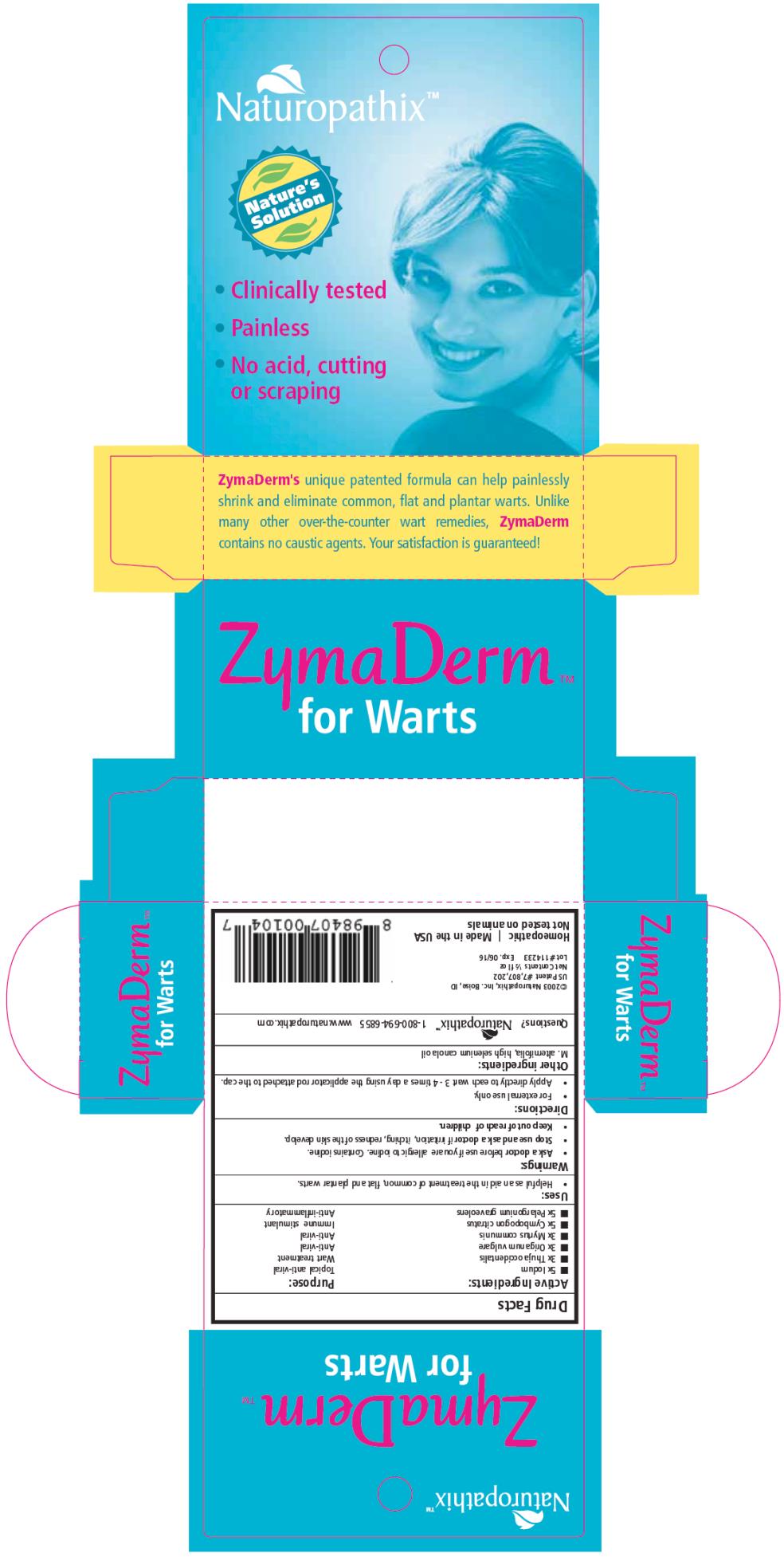 DRUG LABEL: ZymaDerm for Warts
NDC: 69163-4134 | Form: LIQUID
Manufacturer: Naturopathix, Inc.
Category: homeopathic | Type: HUMAN OTC DRUG LABEL
Date: 20210115

ACTIVE INGREDIENTS: IODINE 5 [hp_X]/13 mL; THUJA OCCIDENTALIS WHOLE 3 [hp_X]/13 mL; ORIGANUM VULGARE SUBSP. HIRTUM WHOLE 3 [hp_X]/13 mL; MYRTUS COMMUNIS WHOLE 3 [hp_X]/13 mL; CYMBOPOGON CITRATUS WHOLE 5 [hp_X]/13 mL; PELARGONIUM GRAVEOLENS WHOLE 5 [hp_X]/13 mL
INACTIVE INGREDIENTS: TEA TREE OIL; CANOLA OIL

ZymaDerm for Warts

Drug Facts

Active Ingredient

5x Iodum

Purpose

Topical anti-viral

Active Ingredient

3x Thuja occidentalis

Purpose

Wart treatment anti-viral

Active Ingredient

3x Origanum vulgare

Purpose

Anti-viral

Active Ingredient

3x Myrtus communis

Purpose

Anti-viral

Active Ingredient

5x Cymbopogon citrates

Purpose

Immune stimulant

Active Ingredient

5x Pelargonium graveolens

Purpose

Anti-inflammatory

Uses:

Helpful as an aid in the treatment of common, flat, and plantar warts.

Directions:

Apply 2 – 3 times per day using the applicator rod attached to the cap. To speed wart removal you may use ZymaDerm™ under occlusion. Put a drop on the wart and then a few drops on the inside of a band aid and then cover the wart with the band aid. Do this twice a day for maximum effect. Minimize contact with normal skin as repeated application to normal skin may cause dryness. Not for use in children under 9 mo of age.

KEEP OUT OF REACH OF CHILDREN.

NOT TO BE TAKEN INTERNALLY. CONTAINS IODINE. Discontinue if itching or redness of surrounding skin develops. IF YOU ARE ALLERGIC TO IODINE OR IF YOU ARE PREGNANT CONSULT YOUR PHYSICIAN PRIOR TO USE. If swallowed, give supportive care. Avoid contact with eyes. Clean spills with rubbing alcohol.

Other Ingredients:

M. alternifolia, high selenium canola oil

Distributed by Naturopathix, Inc. Boise, ID 1-800-694-6855

Net Contents ½ fl oz

©2003 Naturopathix, Inc. Boise, ID All rights reserved. Homeopathic

US Patent # 7,807,202

Principal Display Panel

ZymaDerm TM
for Warts